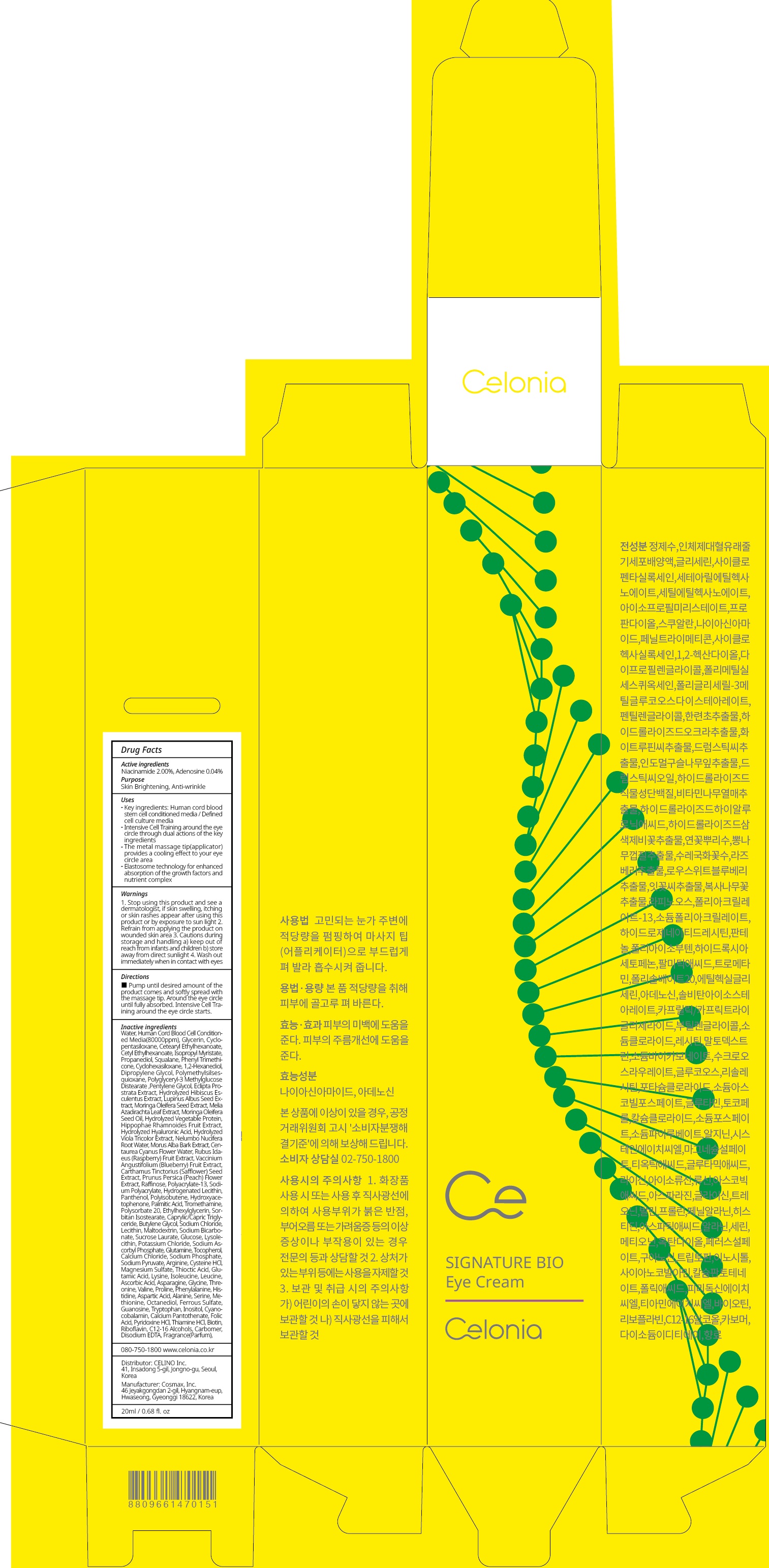 DRUG LABEL: CELONIA SIGNATURE BIO EYE
NDC: 73655-040 | Form: CREAM
Manufacturer: Celino Inc.
Category: otc | Type: HUMAN OTC DRUG LABEL
Date: 20200310

ACTIVE INGREDIENTS: Niacinamide 0.40 g/20 mL; Adenosine 0.008 g/20 mL
INACTIVE INGREDIENTS: Water; Glycerin

ACTIVE INGREDIENT

Active ingredients: Niacinamide 2.00%, Adenosine 0.04%

INACTIVE INGREDIENT

Inactive ingredients:

Water,Human Cord Blood Cell Conditioned Media(80000ppm),Glycerin,Cyclopentasiloxane,Cetearyl Ethylhexanoate,Cetyl Ethylhexanoate,Isopropyl Myristate,Propanediol,Squalane,Phenyl Trimethicone,Cyclohexasiloxane,1,2-Hexanediol,Dipropylene Glycol,Polymethylsilsesquioxane,Polyglyceryl-3 Methylglucose Distearate,Pentylene Glycol,Eclipta Prostrata Extract,Hydrolyzed Hibiscus Esculentus Extract,Lupinus Albus Seed Extract,Moringa Oleifera Seed Extract,Melia Azadirachta Leaf Extract,Moringa Oleifera Seed Oil,Hydrolyzed Vegetable Protein,Hippophae Rhamnoides Fruit Extract,Hydrolyzed Hyaluronic Acid,Hydrolyzed Viola Tricolor Extract,Nelumbo Nucifera Root Water,Morus Alba Bark Extract,Centaurea Cyanus Flower Water,Rubus Idaeus (Raspberry) Fruit Extract,Vaccinium Angustifolium (Blueberry) Fruit Extract,Carthamus Tinctorius (Safflower) Seed Extract,Prunus Persica (Peach) Flower Extract,Raffinose,Polyacrylate-13,Sodium Polyacrylate,Hydrogenated Lecithin,Panthenol,Polyisobutene,Hydroxyacetophenone,Palmitic Acid,Tromethamine,Polysorbate 20,Ethylhexylglycerin,Sorbitan Isostearate,Caprylic/Capric Triglyceride,Butylene Glycol,Sodium Chloride,Lecithin,Maltodextrin,Sodium Bicarbonate,Sucrose Laurate,Glucose,Lysolecithin,Potassium Chloride,Sodium Ascorbyl Phosphate,Glutamine,Tocopherol,Calcium Chloride,Sodium Phosphate,Sodium Pyruvate,Arginine,Cysteine HCl,Magnesium Sulfate,Thioctic Acid,Glutamic Acid,Lysine,Isoleucine,Leucine,Ascorbic Acid,Asparagine,Glycine,Threonine,Valine,Proline,Phenylalanine,Histidine,Aspartic Acid,Alanine,Serine,Methionine,Octanediol,Ferrous Sulfate,Guanosine,Tryptophan,Inositol,Cyanocobalamin,Calcium Pantothenate,Folic Acid,Pyridoxine HCl,Thiamine HCl,Biotin,Riboflavin,C12-16 Alcohols,Carbomer,Disodium EDTA,Fragrance(Parfum)

PURPOSE

Purpose: Skin Brightening, Anti-wrinkle

WARNINGS

1. Stop using this product and see a dermatologist, if skin swelling, itching or skin rashes appear after using this product or by exposure to sun light

2. Refrain from applying the product on wounded skin area

3. Cautions during storage and handling a) keep out of reach from infants and children b) store away from direct sunlight

4. Wash out immediately when in contact with eyes

KEEP OUT OF REACH OF CHILDREN

keep out of reach from infants and children

QUESTIONS

080-750-1800

www.celonia.co.kr

Uses

Key ingredients: Human cord blood stem cell conditioned media / Defined cell culture media
Intensive Cell Training around the eye circle through dual actions of the key ingredients
The metal massage tip(applicator) provides a cooling effect to your eye circle area
Elastosome technology for enhanced absorption of the growth factors and nutrient complex

Directions

Pump until desired amount of the product comes and softly spread with the massage tip. Around the eye circle until fully absorbed. Intensive Cell Training around the eye circle starts.